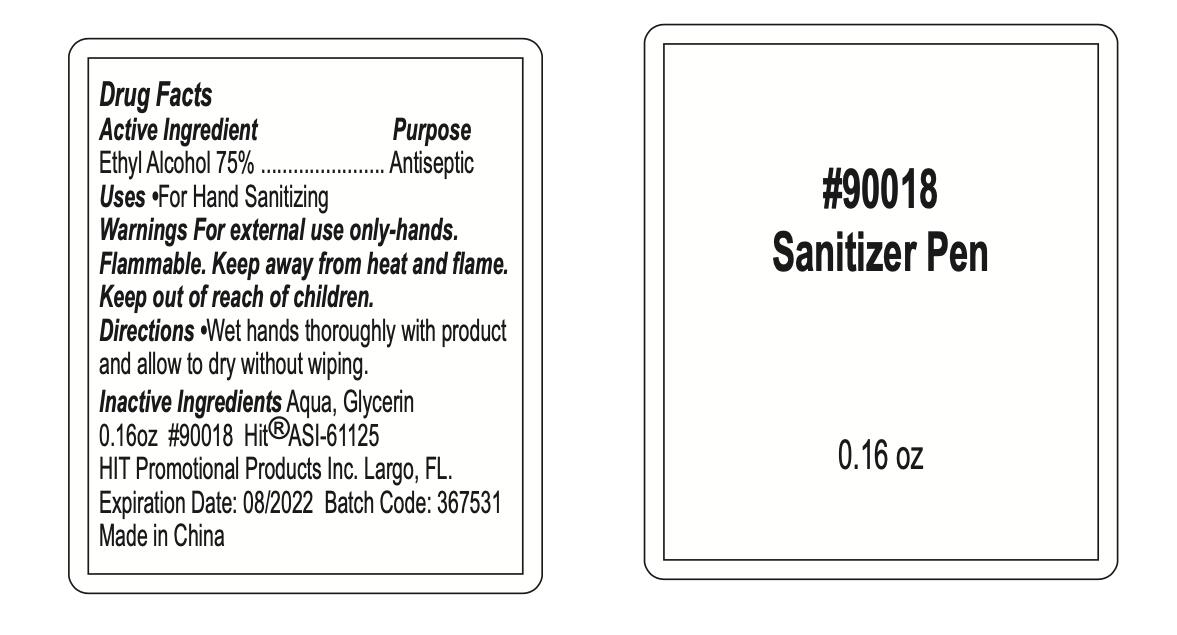 DRUG LABEL: 90018 Sanitizer Pen
NDC: 74274-201 | Form: SPRAY
Manufacturer: Huizhou Bliss Commodity Co., Ltd
Category: otc | Type: HUMAN OTC DRUG LABEL
Date: 20200902

ACTIVE INGREDIENTS: ALCOHOL 75 g/117 mL
INACTIVE INGREDIENTS: WATER; GLYCERIN

74274-201
90018 Sanitizer Pen

Active Ingredient(s)

Ethyl Alcohol 75% (w/w)
75g/117mL

Purpose

Antiseptic

Use

For Hand Sanitizing

Warnings

For external use only-hands.
Flammable. Keep away from heat and flame.

Keep out of reach of children.

Do not use

/

WHEN USING

/

STOP USE

/

Keep out of reach of children.

Directions

Wet hands thoroughly with product and allow to dry without wiping.

Other information

/

Inactive ingredients

Aqua, Glycerin